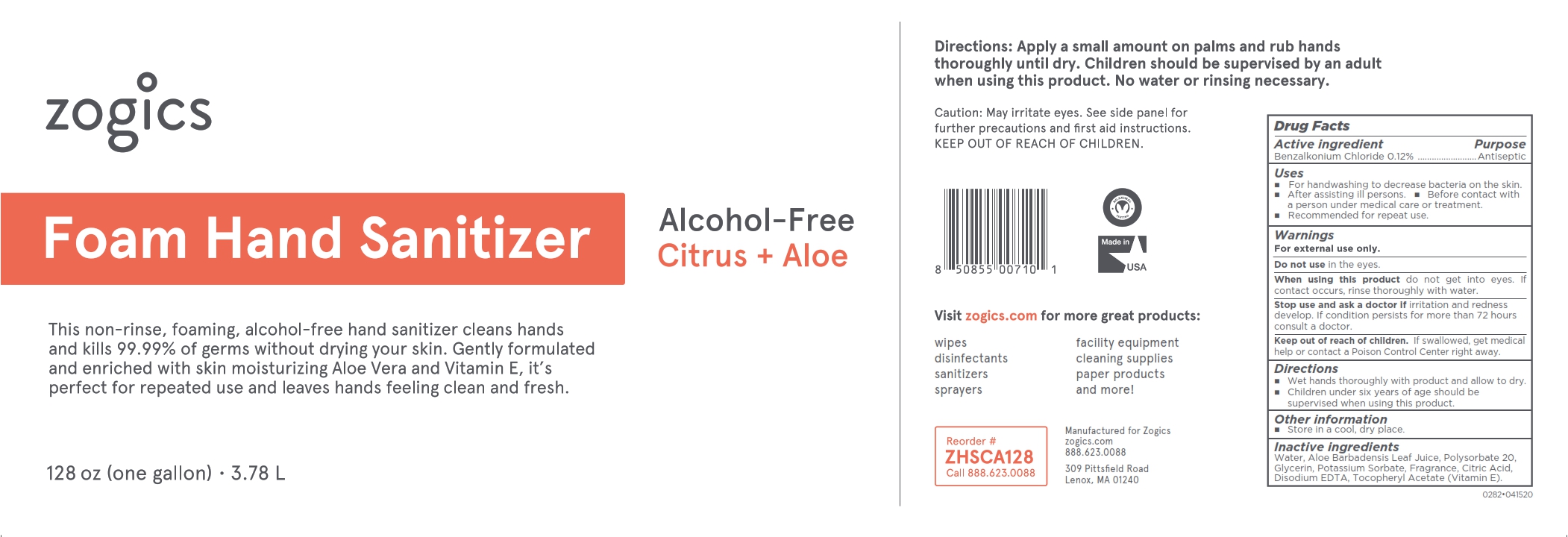 DRUG LABEL: Zogics Foam Hand Sanitizer
NDC: 72202-282 | Form: LIQUID
Manufacturer: Zogics, LLC
Category: otc | Type: HUMAN OTC DRUG LABEL
Date: 20250606

ACTIVE INGREDIENTS: BENZALKONIUM CHLORIDE 0.12 g/100 mL
INACTIVE INGREDIENTS: EDETATE DISODIUM; POTASSIUM SORBATE; WATER; GLYCERIN; CITRIC ACID; ALPHA-TOCOPHEROL ACETATE; ALOE BARBADENSIS LEAF; POLYSORBATE 20

0282-Zogics Foam Hand Sanitizer

Active ingredient

Benzalkonium Chloride 0.12%

Purpose

Antiseptic

Uses

- For handwashing to decrease bacteria on the skin.
- After changing diapers.
- After assisting ill persons.
- Before contact with a person under medical care or treatment.
- Recommended for repeat use.

Warnings

For external use only

Do not use

in the eyes.

When using this product

do not get into eyes. If contact occurs, rinse thoroughly with water.

Stop use and ask a doctor if

irritation and redness develop. If condition persists for more that 72 hours consult a doctor.

Keep out of reach of children

If swallowed, get medical help or contact a Poison Control Center right away.

Directions

- Wet hands thoroughly with product and allow to dry.
- Children under six years of age should be supervised whtn using this product.

Other information

Store in a cook, dry place.

Inactive ingredients

Water, Aloe Barbadensis Leaf Juice, Polysorbate 20, Glycerin, Potassium Sorbate, Fragrance, Citric Acid, Disodium EDTA, Tocopheryl Acetate (Vitamin E).